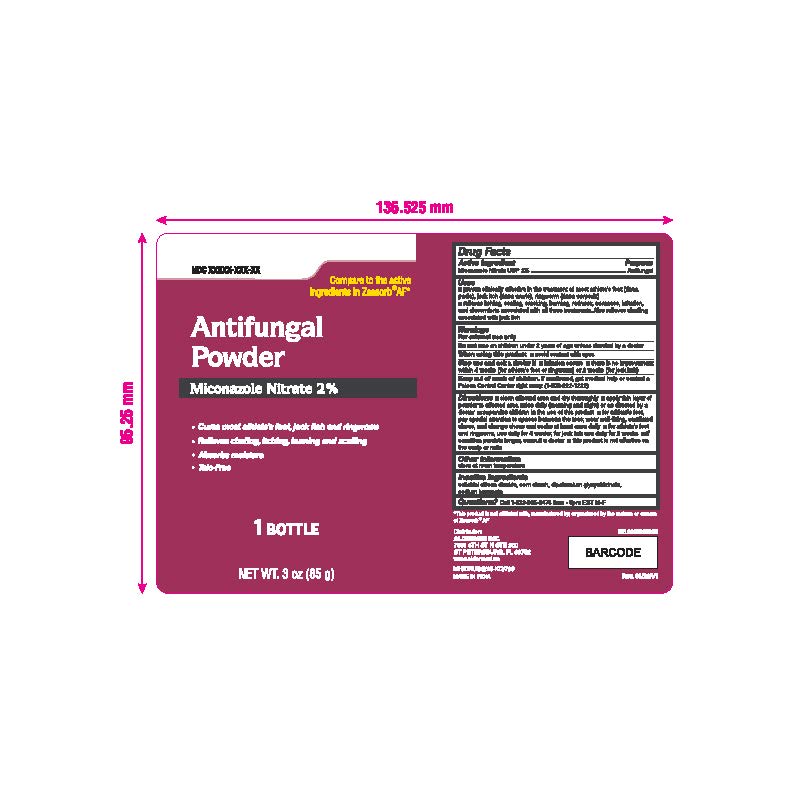 DRUG LABEL: Antifungal Powder
NDC: 87236-012 | Form: POWDER
Manufacturer: Aldermed Inc.
Category: otc | Type: HUMAN OTC DRUG LABEL
Date: 20260212

ACTIVE INGREDIENTS: MICONAZOLE NITRATE 2 g/100 g
INACTIVE INGREDIENTS: SILICON DIOXIDE; STARCH, CORN; DIPOTASSIUM GLYCYRRHIZATE; SODIUM BENZOATE

Antifungal Powder

Active Ingredient

Miconazol Nitrate 2%

Purpose

Antifungal

Uses

• Proven clinically effective in the treatment of most: • athlete's foot • jock itch • ringworm • Relieves itching, scaling, cracking, burning, redness, soreness, irrita-tion, and discomforts associated with all three treatments. Also relieves chaffing associated with jock itch.

Warnings

For external use only.

Do not use on children under 2 years of age unless directed by a doctor

When using this product

Avoid contact with eyes

Stop use and ask a doctor if

■ irritation occurs

■ there is no improvement I within 4 weeks (for athlete's foot or ringworm) or 2 weeks (for jock itch)

Keep Out Of Reach Of Children

Do not let the powder get into your eyes. This product contains talc. Do not breathe in the powder as this may cause irritation of the airways. This is especially important for children and infants. If swallowed, contact a poison control center immediately.

Directions

■ clean affected area and dry thoroughly

■ apply thin layer of powder to affected area twice daily (morning and night) or as direct-ed by a doctor

■ supervise children in the use of this product

■ for athlete's foot pay special attention to space between the toes; wear well-fitting, ventilated shoes and change shoes and socks at least once daily

• for athlete's foot and ringworm, use daily for 4 weeks; for jock itch use daily for 2 weeks

■ if condition persists longer, consult a doctor

•this product is not effective on the scalp or nail

Other information

Store at room temperature

Inactive ingredients

Colloidal silicon dioxide, Corn Starch, Dipotassium Glycyrhizinate, Sodium Benzoate

Questions

Call 1-833-605-84-74 9am-5 pm EST M-F